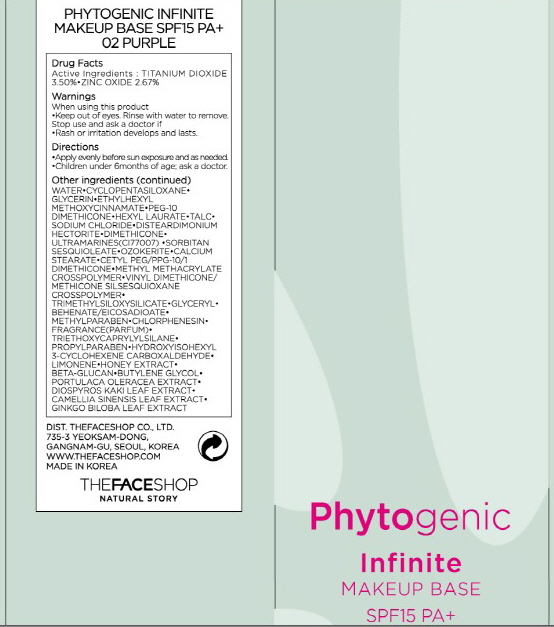 DRUG LABEL: PHYTOGENIC INFINITE MAKEUP BASE
NDC: 51523-030 | Form: CREAM
Manufacturer: THEFACESHOP CO., LTD.
Category: otc | Type: HUMAN OTC DRUG LABEL
Date: 20100930

ACTIVE INGREDIENTS: TITANIUM DIOXIDE 1.23 mL/35 mL; ZINC OXIDE 0.93 mL/35 mL

Drug Facts

Active Ingredients:

TITANIUM DIOXIDE, ZINC OXIDE

Inactive Ingredients:

WATER, CYCLOPENTASILOXANE, GLYCERIN, ETHYLHEXYL METHOXYCINNAMATE, PEG-10 DIMETHICONE, HEXYL LAURATE, TALC, SODIUM CHLORIDE, DISTEARDIMONIUM HECTORITE, DIMETHICONE, ULTRAMARINES, SORBITAN SESQUIOLEATE, OZOKERITE, CALCIUM STEARATE, CETYL PEG/PPG-10/1 DIMETHICONE, METHYL METHACRYLATE CROSSPOLYMER, VINYL DIMETHICONE/METHICONE SILSESQUIOXANE CROSSPOLYMER, TRIMETHYLSILOXYSILICATE, GLYCERYL, BEHENATE/EICOSADIOATE, METHYLPARABEN, CHLORPHENESIN, FRAGRANCE, TRIETHOXYCAPRYLYLSILANE, PROPYLPARABEN, HYDROXYISOHEXYL 3-CYCLOHEXENE CARBOXALDEHYDE, LIMONENE, HONEY EXTRACT, BETA GLUCAN, BUTYLENE GLYCOL, PORTULACA OLERACEA EXTRACT, DIOSPYROS KAKI LEAF EXTRACT, CAMELLIA SINENSIS LEAF EXTRACT, GINKGO BILOBA LEAF EXTRACT

Warnings:
When using this product
Keep out of eyes. Rinse with water to remove.
Stop use and ask a doctor if
Rash or irritation develops and lasts.
Directions:
Apply evenly before sun exposure and as needed.
Children under 6months of age; ask a doctor.